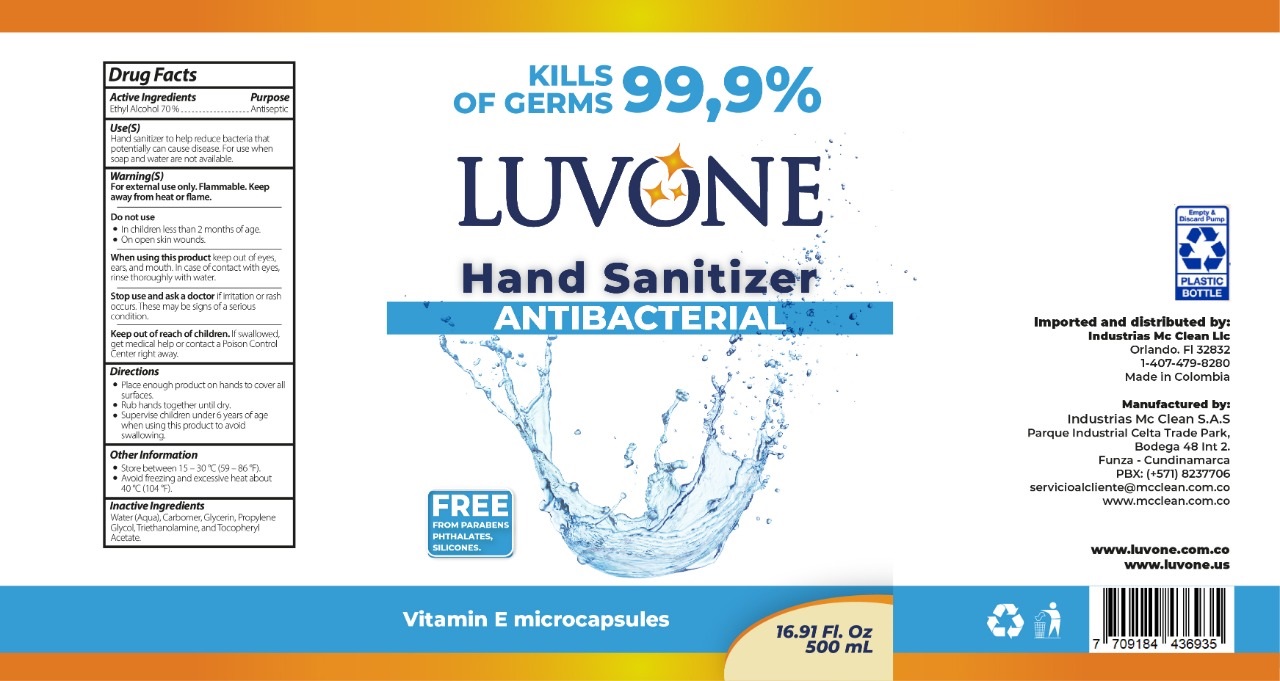 DRUG LABEL: Luvone hand sanitizer
NDC: 80683-006 | Form: LIQUID
Manufacturer: INDUSTRIAS MC CLEAN S A S
Category: otc | Type: HUMAN OTC DRUG LABEL
Date: 20210714

ACTIVE INGREDIENTS: ALCOHOL 70 mL/100 mL
INACTIVE INGREDIENTS: WATER; CARBOMER HOMOPOLYMER, UNSPECIFIED TYPE; GLYCERIN; PROPYLENE GLYCOL; TROLAMINE; .ALPHA.-TOCOPHEROL ACETATE

Luvone liquid hand sanitizer

Active Ingredients

Ethyl Alcohol 70%

Purpose

Antiseptic

Use(S)

Hand sanitizer to help reduce bacteria that potentially can cause disease. For use when soap and water are not available.

Warning(S)

For external use only. Flammable. Keep away from heat or flame.

Do not use

- In children less than 2 months of age.
- On open skin wounds.

When using this product

keep out of eyes, ears, and mouth. In case of contact with eyes, rinse thoroughly with water.

Stop use and ask a doctor

If irritation or rash occurs. These may be signs of a serious condition.

Keep out of reach of children.

If swallowed, get medical help or contact a Poison Control Center right away.

Directions

- Place enough product on hands to cover all surfaces.
- Rub hands together until dry.
- Supervise children under 6 years of age when using this product to avoid swallowing.

Other Information

- Store between 15-30 °C (59-86 °F).
- Avoid freezing and excessive heat about 40 °C (104° F).

Inactive Ingredients

Water (Aqua), Carbomer, Glycerin, Propylene Glycol, Triethanolamine, and Tocopheryl Acetate.